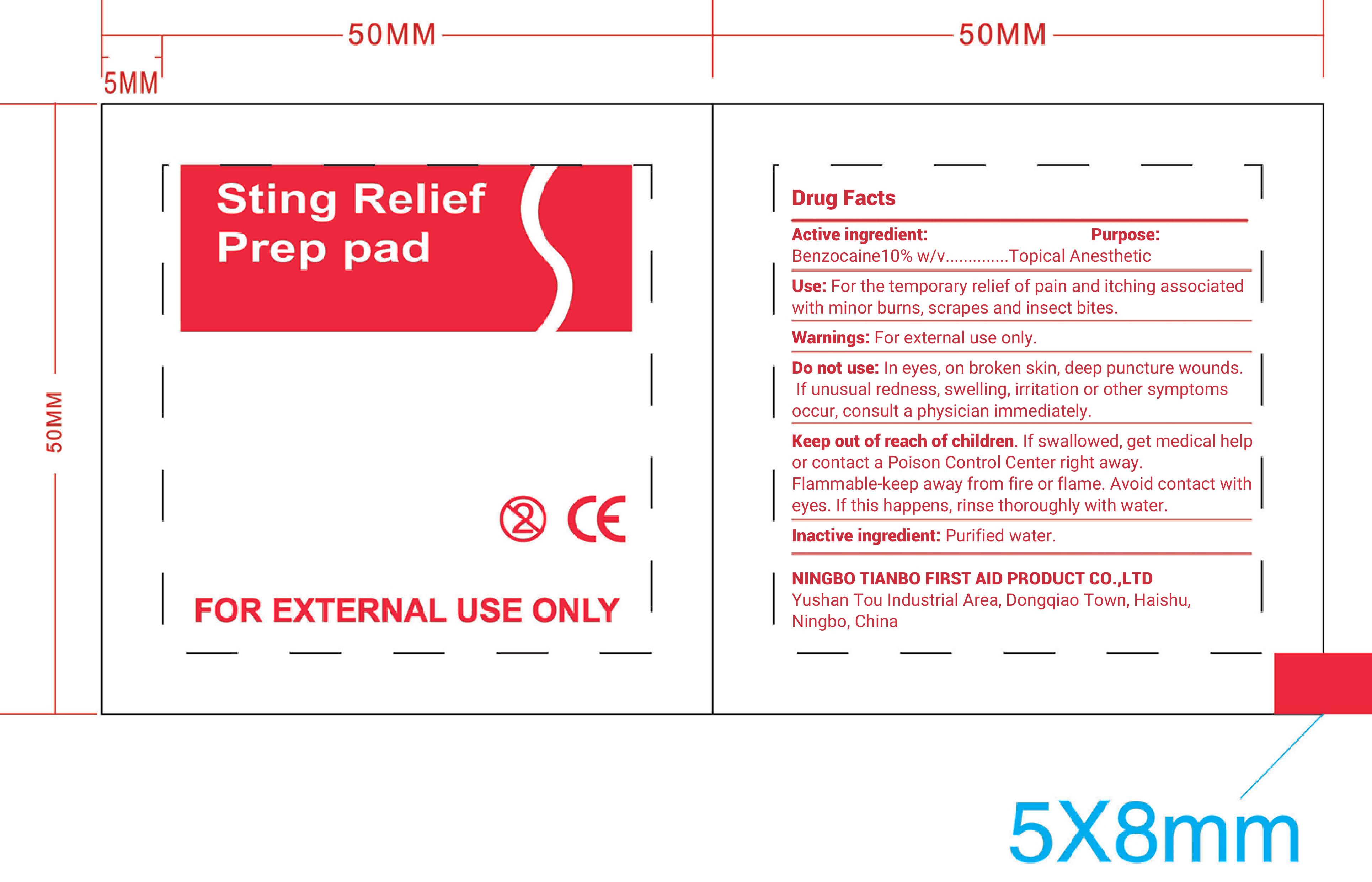 DRUG LABEL: Sting Relief Prep Pad
NDC: 73288-004 | Form: SOLUTION
Manufacturer: NINGBO TIANBO FIRST AID PRODUCT CO., LTD.
Category: otc | Type: HUMAN OTC DRUG LABEL
Date: 20260112

ACTIVE INGREDIENTS: BENZOCAINE 10 g/100 g
INACTIVE INGREDIENTS: WATER

73288-004

Active Ingredient: Benzocaine 10% w/v

Purpose: Topical Anesthetic

INDICATIONS AND USAGE

Uses: For temporary relief of pain and itching associated with minor burns, scrapes, and insect bites

Warnings:

For external use only

Do not use: In the eyes, on broken skin, deep puncture wounds. I f unusal redness, swelling, irritation, or other symptoms occur, consult a physician immediately.

Keep out of reach of children. If swallowed, get medical help or contact a Poison Control Center right away

Flammable. Keep away from fire or flame. Avoid contact with eyes. If this happens, rinse thoroughly with water.

DOSAGE AND ADMINISTRATION

Directions: Wipe injection site vigorously and discard

Inactive Ingredient

Purified Water